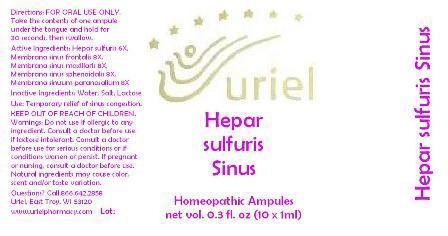 DRUG LABEL: Hepar sulfuris Sinus
NDC: 48951-5049 | Form: LIQUID
Manufacturer: Uriel Pharmacy Inc.
Category: homeopathic | Type: HUMAN PRESCRIPTION DRUG LABEL
Date: 20140402

ACTIVE INGREDIENTS: CALCIUM SULFIDE 6 [hp_X]/1 mL; BOS TAURUS NASAL MUCOSA 8 [hp_X]/1 mL
INACTIVE INGREDIENTS: WATER; SODIUM CHLORIDE; LACTOSE

Hepar sulfuris Sinus

INDICATIONS AND USAGE

Directions: FOR ORAL USE ONLY.

DOSAGE AND ADMINISTRATION

Take the contents of one ampule
under the tongue and hold for
30 seconds, then swallow.

ACTIVE INGREDIENT

Active Ingredients: Hepar sulfuris 6X, Membrana sinus frontalis 8X,
Membrana sinus maxillaris 8X,
Membrana sinus sphenoidalis 8X,
Membrana sinuum paranasalium 8X

Inactive Ingredients: Water, Salt, Lactose

PURPOSE

Use: Temporary relief of sinus congestion.

KEEP OUT OF REACH OF CHILDREN.

WARNINGS

Warnings: Do not use if allergic to any ingredient. Consult a doctor before use if lactose intolerant. Consult a doctor before use for serious conditions or if conditions worsen or persist. If pregnant or nursing, consult a doctor before use. Natural ingredients may cause color, scent and/or taste variation.

Questions? Call 866.642.2858
Uriel, East Troy, WI 53120
www.urielpharmacy.com